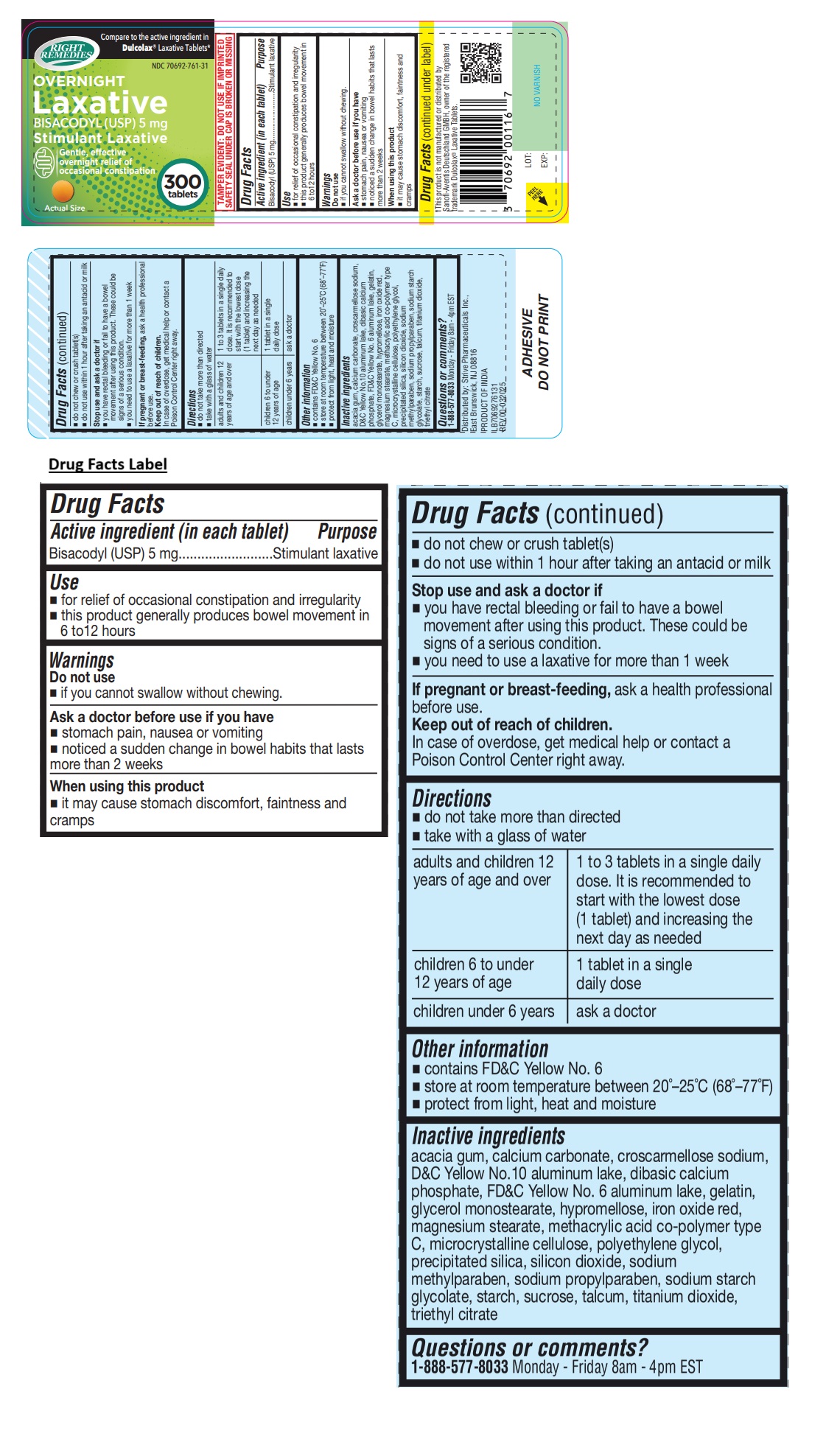 DRUG LABEL: RIGHT REMEDIES OVERNIGHT Laxative
NDC: 70692-761 | Form: TABLET
Manufacturer: Strive Pharmaceuticals Inc.
Category: otc | Type: HUMAN OTC DRUG LABEL
Date: 20250425

ACTIVE INGREDIENTS: BISACODYL 5 mg/1 1
INACTIVE INGREDIENTS: ACACIA; CALCIUM CARBONATE; CROSCARMELLOSE SODIUM; D&C YELLOW NO. 10 ALUMINUM LAKE; ANHYDROUS DIBASIC CALCIUM PHOSPHATE; FD&C YELLOW NO. 6 ALUMINUM LAKE; GELATIN, UNSPECIFIED; GLYCERYL MONOSTEARATE; HYPROMELLOSE, UNSPECIFIED; FERRIC OXIDE RED; MAGNESIUM STEARATE; METHACRYLIC ACID AND ETHYL ACRYLATE COPOLYMER; MICROCRYSTALLINE CELLULOSE; POLYETHYLENE GLYCOL, UNSPECIFIED; SILICON DIOXIDE; METHYLPARABEN SODIUM; PROPYLPARABEN SODIUM; SODIUM STARCH GLYCOLATE TYPE A; STARCH, CORN; SUCROSE; TALC; TITANIUM DIOXIDE; TRIETHYL CITRATE

RIGHT REMEDIES OVERNIGHT Laxative BISACODYL (USP) 5 mg

Active ingredient (in each tablet)

Bisacodyl (USP) 5 mg

Purpose

Stimulant laxative

Use

• for relief of occasional constipation and irregularity
• this product generally produces bowel movement in 6 to12 hours

Warnings

Do not use
• if you cannot swallow without chewing.

Ask a doctor before use if you have
• stomach pain, nausea or vomiting
• noticed a sudden change in bowel habits that lasts more than 2 weeks

When using this product
• it may cause stomach discomfort, faintness and cramps
• do not chew or crush tablet(s)
• do not use within 1 hour after taking an antacid or milk

Stop use and ask a doctor if
• you have rectal bleeding or fail to have a bowel movement after using this product. These could be signs of a serious condition.
• you need to use a laxative for more than 1 week

If pregnant or breast-feeding, ask a health professional before use.

Keep out of reach of children.
In case of overdose, get medical help or contact a Poison Control Center right away.

Directions

• do not take more than directed
• take with a glass of water

adults and children 12 years of age and over | 1 to 3 tablets in a single daily dose. It is recommended to start with the lowest dose (1 tablet) and increasing the next day as needed
children 6 to under 12 years of age | 1 tablet in a single daily dose
children under 6 years | ask a doctor

Other information

• contains FD&C Yellow No. 6
• store at room temperature between 20˚–25˚C (68˚–77˚F)
• protect from light, heat and moisture

Inactive ingredients

acacia gum, calcium carbonate, croscarmellose sodium, D&C Yellow No.10 aluminum lake, dibasic calcium phosphate, FD&C Yellow No. 6 aluminum lake, gelatin, glycerol monostearate, hypromellose, iron oxide red, magnesium stearate, methacrylic acid co-polymer type C, microcrystalline cellulose, polyethylene glycol, precipitated silica, silicon dioxide, sodium methylparaben, sodium propylparaben, sodium starch glycolate, starch, sucrose, talcum, titanium dioxide, triethyl citrate

Questions or comments?

1-888-577-8033 Monday - Friday 8am - 4pm EST

Compare to the active ingredient in Dulcolax® Laxative Tablets*

Gentle, effective
overnight relief of
occasional constipation

TAMPER EVIDENT: DO NOT USE IF IMPRINTED SAFETY SEAL UNDER CAP IS BROKEN OR MISSING

*This product is not manufactured or distributed by Sanofi-Aventis Deutschland GMBH, owner of the registered trademark Dulcolax® Laxative Tablets.

Distributed by: Strive Pharmaceuticals Inc.,
East Brunswick, NJ 08816

PRODUCT OF INDIA